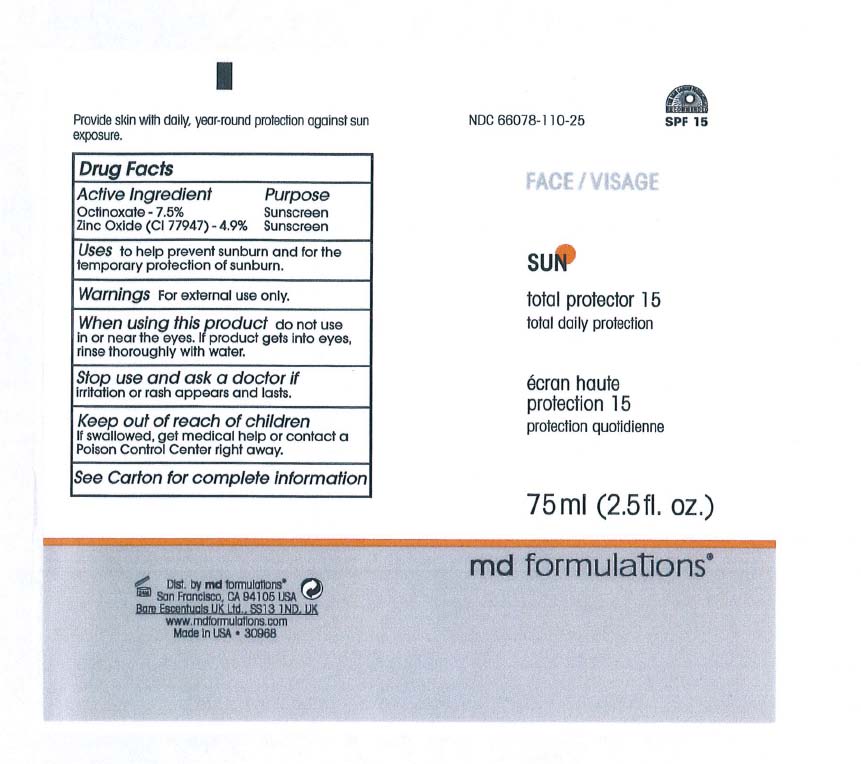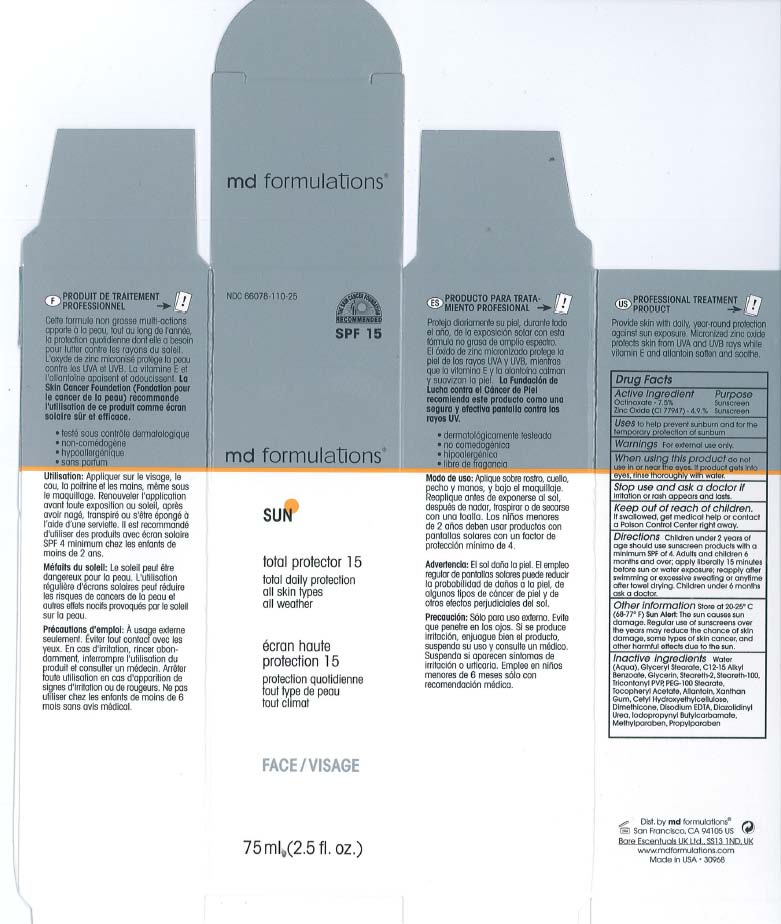 DRUG LABEL: Total Protrector 15
                
NDC: 66078-110 | Form: CREAM
Manufacturer: MD Formulation
Category: otc | Type: HUMAN OTC DRUG LABEL
Date: 20120731

ACTIVE INGREDIENTS: Octinoxate 7.5 g/100 g; Zinc Oxide 4.9 g/100 g
INACTIVE INGREDIENTS: Water; Glycerin; ALLANTOIN; EDETATE DISODIUM; XANTHAN GUM; CETYL HYDROXYETHYLCELLULOSE (350000 MW); DIAZOLIDINYL UREA; IODOPROPYNYL BUTYLCARBAMATE; GLYCERYL STEARATE SE; STEARETH-2; PEG-100 STEARATE; STEARETH-100; TRIACONTANYL PVP (WP-660); .ALPHA.-TOCOPHEROL ACETATE; PROPYLPARABEN

Sun Total Protector 15

ACTIVE INGREDIENT

Octinoxate - 7.5% Sunscreen
Zink Oxide - 4.9% Sunscreen

When using this product do not use in or near the eyes.If product gets into eyes, rlnse thoroughly with water.

Warnings: For external use only.

Stop use and ask a doctor if Irritation or rash appears and lasls.

Keep out of reach of children. If swallowed , get medical help or contact a Poison Control Center right away.

DOSAGE AND ADMINISTRATION

Directions: Children under 2 years of age should use sunscreen products with a minimum SPF of 4.
Adult and children 6 months and over: apply liberally 15 minutes before sun or water exposure; reapply after swimming or excessive sweating or anytime after towel drying . Children under 6 months ask a doctor.

Other information store at 20.25C (68-770 F)
Sun Alert: The sun causes sun damage. Regular use of sunscreens over the years may reduce the chance of skIn damage, some types of skin cancer, and other harmful effects due to the sun.

INACTIVE INGREDIENT

Inactive ingredients: Water (Aqua), Glyceryl Stearate, C12-15 Alkyl Benzoate, GlycerIn, Steareth-2, Steareth-100, Tricontanyl PVP, PEG-100 Stearate, Tocopheryl Acetate, Allantoin, Xanthan Gum, Cetyl Hydroxyelhylcellulose, Dimethicone, Disodium EDTA, Diazolidinyl Urea, lodopropynyl Butylcarbamate, Methylparaben. Propylparaben.